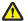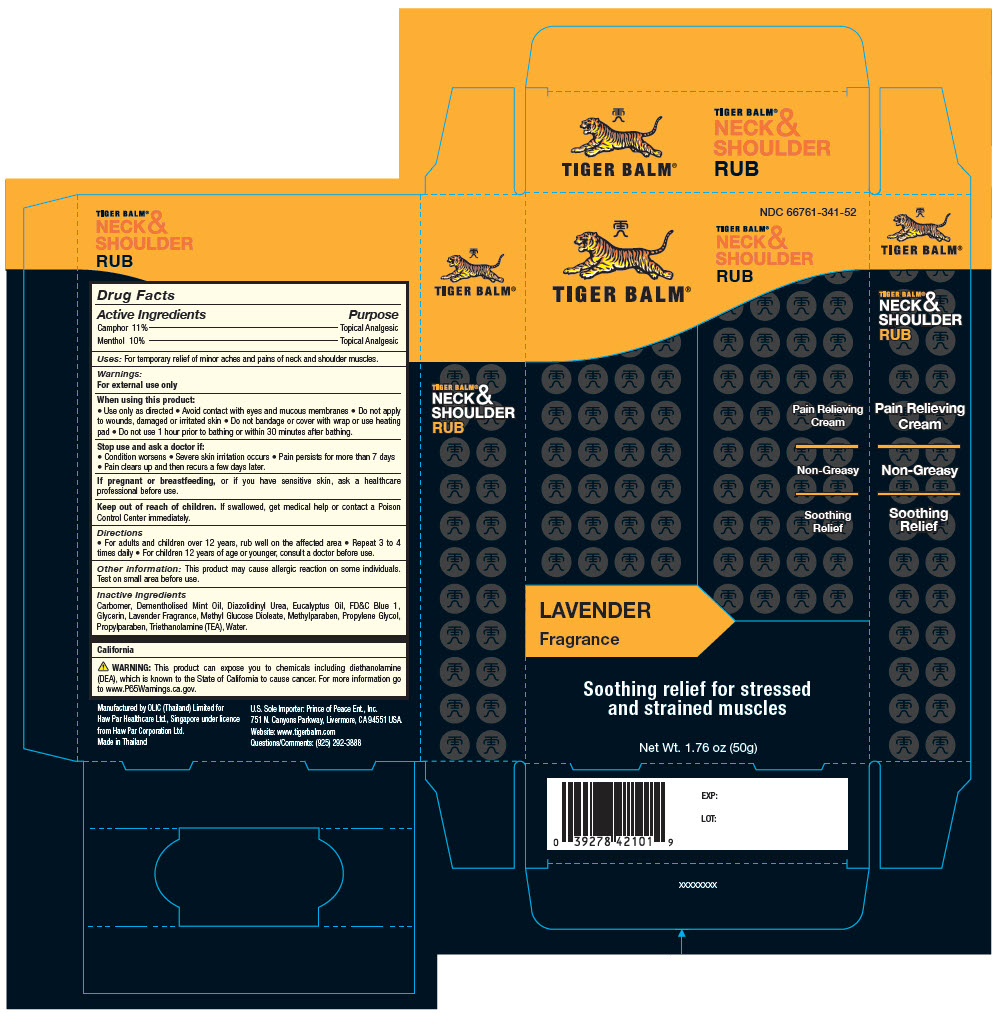 DRUG LABEL: Tiger Balm 
NDC: 66761-341 | Form: CREAM
Manufacturer: Haw Par Healthcare Ltd.
Category: otc | Type: HUMAN OTC DRUG LABEL
Date: 20250909

ACTIVE INGREDIENTS: Camphor (Synthetic) 11 mg/1 g; Menthol, Unspecified Form 10 mg/1 g
INACTIVE INGREDIENTS: Carbomer Homopolymer, Unspecified Type; Diazolidinyl Urea; Eucalyptus oil; FD&C Blue No. 1; Glycerin; Peg-120 Methyl Glucose Dioleate; Methylparaben; Propylene Glycol; Propylparaben; Trolamine; Water

TIGER BALM®
NECK &
SHOULDER
RUB

Drug Facts

ACTIVE INGREDIENT

Active Ingredients | Purpose
Camphor 11% | Topical Analgesic
Menthol 10% | Topical Analgesic

Uses

For temporary relief of minor aches and pains of neck and shoulder muscles.

Warnings

For external use only

When using this product

- Use only as directed
- Avoid contact with eyes and mucous membranes
- Do not apply to wounds, damaged or irritated skin
- Do not bandage or cover with wrap or use heating pad
- Do not use 1 hour prior to bathing or within 30 minutes after bathing.

Stop use and ask a doctor if

- Condition worsens
- Severe skin irritation occurs
- Pain persists for more than 7 days
- Pain clears up and then recurs a few days later.

PREGNANCY OR BREAST FEEDING

If pregnant or breastfeeding, or if you have sensitive skin, ask a healthcare professional before use.

Keep out of reach of children. If swallowed, get medical help or contact a Poison Control Center immediately.

Directions

- For adults and children over 12 years, rub well on the affected area
- Repeat 3 to 4 times daily
- For children 12 years of age or younger, consult a doctor before use.

Other information

This product may cause allergic reaction on some individuals. Test on small area before use.

Inactive Ingredients

Carbomer, Dementholised Mint Oil, Diazolidinyl Urea, Eucalyptus Oil, FD&C Blue 1, Glycerin, Lavender Fragrance, Methyl Glucose Dioleate, Methylparaben, Propylene Glycol, Propylparaben, Triethanolamine (TEA), Water.

California

WARNING: This product can expose you to chemicals including diethanolamine (DEA), which is known to the State of California to cause cancer. For more information go to www.P65Warnings.ca.gov.

Questions/Comments

(925) 292-3888

Manufactured by OLIC (Thailand) Limited for
Haw Par Healthcare Ltd., Singapore under licence
from Haw Par Corporation Ltd.

PRINCIPAL DISPLAY PANEL - 50 g Tube Carton

NDC 66761-341-52

TIGER BALM®

TIGER BALM®
NECK &
SHOULDER
RUB

Pain Relieving
Cream

Non-Greasy

Soothing
Relief

LAVENDER
Fragrance

Soothing relief for stressed
and strained muscles

Net Wt. 1.76 oz (50g)